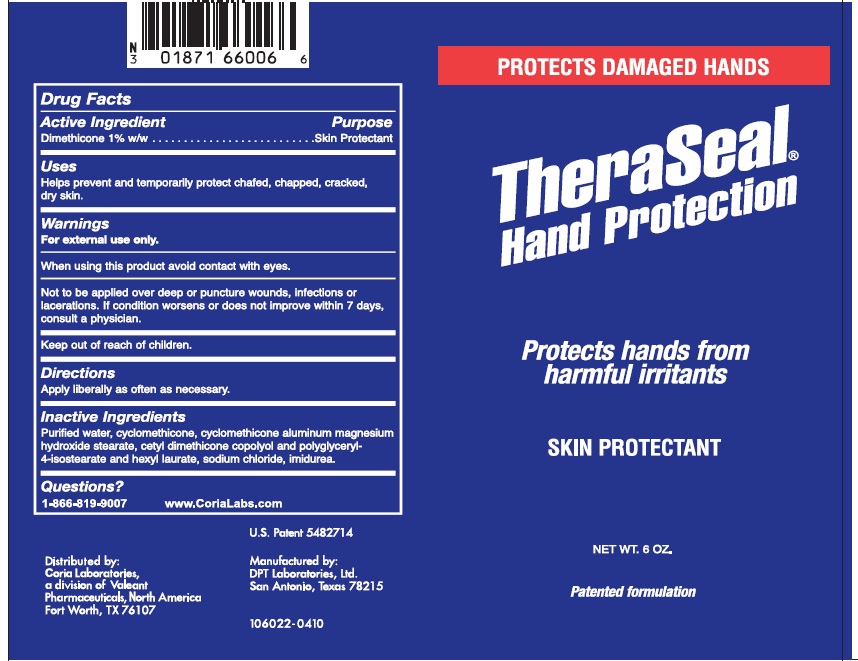 DRUG LABEL: TheraSeal
NDC: 0187-1660 | Form: CREAM
Manufacturer: Bausch Health US, LLC
Category: otc | Type: HUMAN OTC DRUG LABEL
Date: 20241017

ACTIVE INGREDIENTS: DIMETHICONE 1.7 g/170.1 g
INACTIVE INGREDIENTS: WATER; CYCLOMETHICONE; POLYGLYCERYL-4 ISOSTEARATE; HEXYL LAURATE; SODIUM CHLORIDE; IMIDUREA

TheraSeal Hand Protection

Drug Facts

Active Ingredient

Dimethicone 1% w/w

Purpose

Skin Protectant

Uses

Helps prevent and temporarily protect chafed, chapped, cracked, dry skin.

Warnings

For external use only.

When using this product avoid contact with eyes.

Not to be applied over deep or puncture wounds, infections or lacerations. If condition worsens or does not improve within 7 days, consult a physician.

Keep out of reach of children.

Directions

Apply liberally as often as necessary.

Inactive Ingredients

Purified water, cyclomethicone, cyclomethicone aluminum magnesium hydroxide stearate, cetyl dimethicone copolyol and polyglyceryl-4-isostearate and hexyl laurate, sodium chloride, imidurea.

Questions?

1-866-819-9007
www.CoriaLabs.com

U.S. Patent 5482714

Distributed by: Coria Laboratories, a division of Valeant Pharmaceuticals, North America, Fort Worth, TX 76107

Manufactured by: DPT Laboratories, Ltd., San Antonio, Texas 78215

106022-0410

PRINCIPAL DISPLAY PANEL - 6 ounce label

PROTECTS DAMAGED HANDS

TheraSeal®
Hand Protection

Protects hands from
harmful irritants

SKIN PROTECTANT

NET WT. 6 OZ.

Patented formulation